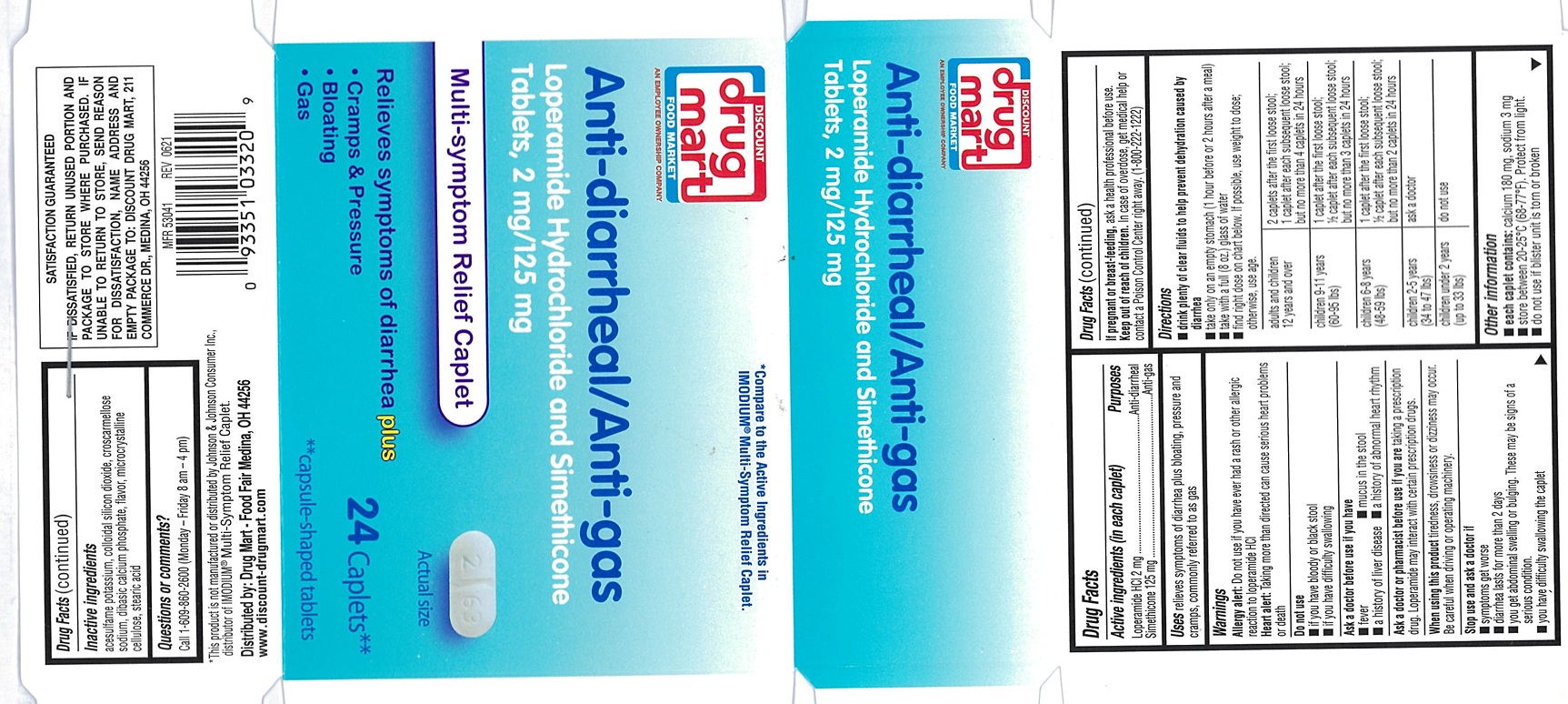 DRUG LABEL: Anti-Diarrheal/Anti-Gas
NDC: 53943-263 | Form: TABLET
Manufacturer: Discount Drug Mart, Inc
Category: otc | Type: Human OTC Drug Label
Date: 20250227

ACTIVE INGREDIENTS: LOPERAMIDE HYDROCHLORIDE 2 mg/1 1; DIMETHICONE 125 mg/1 1
INACTIVE INGREDIENTS: ACESULFAME POTASSIUM; SILICON DIOXIDE; CROSCARMELLOSE SODIUM; ANHYDROUS DIBASIC CALCIUM PHOSPHATE; MICROCRYSTALLINE CELLULOSE; STEARIC ACID

Anti-diarrheal/ Anti-gas Multi-Symptom Relief

ACTIVE INGREDIENTS (in each caplet)

Loperamide HCl 2 mg

Simethicone 125 mg

PURPOSE

Anti-diarrheal

Anti-gas

USE(S)

relieves symptoms of diarrhea plus bloating, pressure and cramps, commonly referred to as gas

WARNINGS

Allergy alert: Do not use if you have ever had a rash or other allergic reaction to loperamide HCl

Heart alert: Taking more than directed can cause serious heart problems or death

DO NOT USE

- if you have bloody or black stool
- if you have difficulty swallowing

ASK A DOCTOR BEFORE USE IF THE CHILD HAS

- fever
- mucus in the stool
- a history of liver disease
- a history of abnormal heart rhythm

ASK A DOCTOR OR PHARMACIST BEFORE USE IF YOU ARE

taking a prescription drug. Loperamide may interact with certain prescription drugs.

WHEN USING THIS PRODUCT

tiredness, drowsiness or dizziness may occur. Be careful when driving or operating machinery.

STOP USE AND ASK DOCTOR IF

- symptoms get worse
- diarrhea lasts for more than 2 days
- you get abdominal swelling or bulging. These may be signs of a serious condition.
- you have difficulty swallowing the caplet

IF PREGNANT OR BREAST FEEDING,

ask a health professional before use.

KEEP OUT OF REACH OF CHILDREN

In case of overdose, get medical help or contact a Poison Control Center right away. (1-800-222-1222)

DIRECTIONS

- drink plenty of clear fluids to help prevent dehydration caused by diarrhea
- take only on an empty stomach (1 hour before or 2 hours after a meal)
- take with a full (8 oz.) glass of water
- find right dose on chart below. If possible, use weight to dose; otherwise, use age.
  adults and children 12 years and over | 2 caplets after the first loose stool; 1 caplet after each subsequent loose stool; but no more than 4 caplets in 24 hours
  children 9-11 years (60-95 lbs) | 1 caplet after the first loose stool; ½ caplet after each subsequent loose stool; but no more than 3 caplets in 24 hours
  children 6-8 years (48-59 lbs) | 1 caplet after the first loose stool; ½ caplet after each subsequent loose stool; but no more than 2 caplets in 24 hours
  children 2-5 years (34 to 47 lbs) | ask a doctor
  children under 2 years (up to 33 lbs) | do not use

OTHER INFORMATION

- each caplet contains: calcium 180 mg, sodium 3 mg
- store between 20-25°C (68-77°F). Protect from light.
- do not use if blister unit is torn or broken

INACTIVE INGREDIENTS

acesulfame potassium, colloidal silicon dioxide, croscarmellose sodium, dibasic calcium phosphate, flavor, microcrystalline cellulose, stearic acid

QUESTIONS OR COMMENTS

Call 1-609-860-2600 (Monday-Friday 8 am- 4 pm)

PRINCIPAL DISPLAY PANEL

*Compare to the Active Ingredients in IMODIUM® Multi-symptom Relief Caplet.

DISCOUNT drug mart

FOOD FAIR

Anti-diarrheal/Anti-gas

Loperamide Hydrochloride and Simethicone

Tablets, 2 mg/125 mg

Multi-symptom Relief Caplet

Relieves Symptoms of Diarrhea Plus

- Cramps & Pressure
- Bloating
- Gas

24 Caplets**

**Capsule-Shaped Tablets

Harris Teeter™

NDC 69256-265-73

MULTI-SYMPTOM RELIEF

ANTI-DIARRHEAL/ANTI-GAS

Loperamide Hydrochloride and Simethicone

Tablets, 2 mg/125 mg

Relieves Symptoms of Diarrhea Plus

Cramps & Pressure

Bloating, Gas

Compare to the active ingredients in Imodium®

Multi-Symptom Relief Caplet*

24 Caplets**

**Capsule-Shaped Tablets